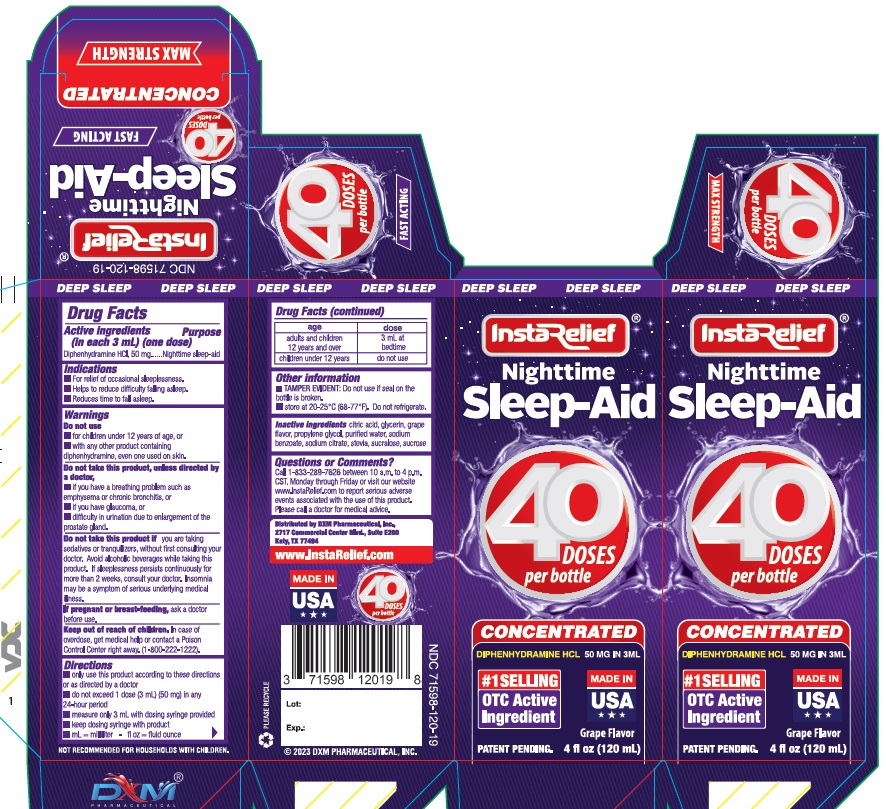 DRUG LABEL: InstaRelief Nighttime Sleep Aid
NDC: 71598-120 | Form: LIQUID
Manufacturer: DXM Pharmacuetical, Inc.
Category: otc | Type: HUMAN OTC DRUG LABEL
Date: 20251006

ACTIVE INGREDIENTS: DIPHENHYDRAMINE HYDROCHLORIDE 50 mg/3 mL
INACTIVE INGREDIENTS: ANHYDROUS CITRIC ACID; GLYCERIN; PROPYLENE GLYCOL; WATER; SODIUM BENZOATE; SODIUM CITRATE; STEVIA LEAF; SUCRALOSE; SUCROSE

Active ingredient

(in each 3mL) (one dose) Diphenhydramine HCI, 50 mg

Purpose

Nighttime sleep-aid

Uses

- For relief of occasional sleeplessness.
- Helps to reduce difficulty falling asleep.
- Reduces time to fall asleep. Warnings

Warning

Do not use

- for children under 12 years of age, or
- with any other product containing diphenhydramine, even one used on skin.

Do not take this product, unless directed by a doctor

- if you have a breathing problem such as emphysema or chronic bronchitis, or
- if you have glaucoma, or
- difficulty in urination due to enlargement of the prostate gland.

Do not take this product ifyou are taking sedatives or tranquilizers, without first consulting your doctor. Avoid alcoholic beverages while taking this product. If sleeplessness persists continuously for more than 2 weeks, consult your doctor. Insomnia may be a symptom of serious underlying medical illness.

If pregnant or breast-feeding, ask a doctor before use.

Keep out of reach of children.In case of overdose, get medical help or contact a Poison Control Center right away. (1-800-222-1222)

Directions

- only use this product according to these directions or as directed by a doctor
- do not exceed 1 dose (3 mL) (50 mg) in any24-hour period
- measure only 3 mL with dosing syringe provided
- keep dosing syringe with product
- mL = milliliter - fl oz = fluid ounce

age | dose
adults and children 12 years and over | 3mL at bedtime
children under 12 years | do not use

Other information

TAMPER EVIDENT: Do not use if seal on the bottle is broken.
store at 20-25°C (68-77°F). Do not refrigerate.

Inactive ingredients

citric acid, glycerin, grape flavor, propylene glycol, purified water, sodium benzoate, sodium citrate, stevia, sucralose, sucrose

Questions or comments?

Call 1-833-289-7626 between 10 a.m. to 4 p.m. CST, Monday through Friday or visit our website www.InstaRelief.com to report serious adverse events associated with the use of this product. Please call a doctor for medical advice.